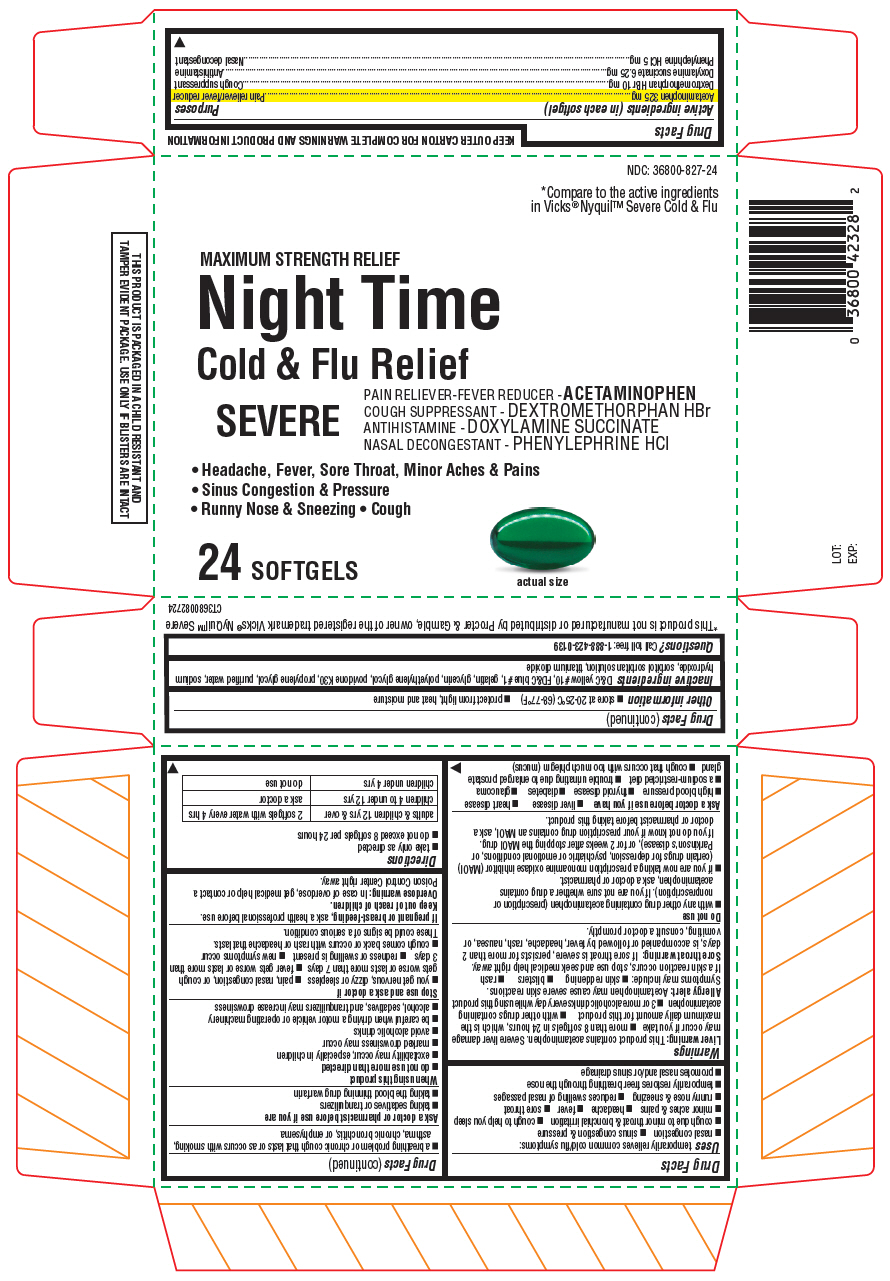 DRUG LABEL: Cold and Flu Severe Nighttime
NDC: 36800-848 | Form: CAPSULE, LIQUID FILLED
Manufacturer: TOPCO ASSOCIATES LLC
Category: otc | Type: HUMAN OTC DRUG LABEL
Date: 20230118

ACTIVE INGREDIENTS: Acetaminophen 325 mg/1 1; Dextromethorphan Hydrobromide 10 mg/1 1; Doxylamine Succinate 6.5 mg/1 1; PHENYLEPHRINE HYDROCHLORIDE 5 mg/1 1
INACTIVE INGREDIENTS: D&C YELLOW NO. 10; FD&C Blue NO. 1; Gelatin, Unspecified; Glycerin; Polyethylene Glycol, Unspecified; Povidone K30; Propylene Glycol; Water; Sodium Hydroxide; Titanium Dioxide

Cold and Flu Severe Nighttime

Drug Facts

ACTIVE INGREDIENT

PURPOSE

Active ingredients (in each softgel) | Purposes
Acetaminophen 325 mg | Pain reliever/fever reducer
Dextromethorphan HBr 10 mg | Cough suppressant
Doxylamine succinate 6.25 mg | Antihistamine
Phenylephrine HCl 5 mg | Nasal decongestant

Uses

temporarily relieves common cold/flu symptoms:

- nasal congestion
- sinus congestion & pressure
- cough due to minor throat & bronchial irritation
- cough to help you sleep
- minor aches & pains
- headache
- fever
- sore throat
- runny nose & sneezing
- reduces swelling of nasal passages
- temporarily restores freer breathing through the nose
- promotes nasal and/or sinus drainage

Warnings

Liver warning

This product contains acetaminophen. Severe liver damage may occur if you take

- more than 8 softgels in 24 hours, which is the maximum daily amount for this product
- with other drugs containing acetaminophen
- 3 or more alcoholic drinks every day while using this product

Allergy alert

Acetaminophen may cause severe skin reactions. Symptoms may include:

- skin reddening
- blisters
- rash

If a skin reaction occurs, stop use and seek medical help right away.

Sore throat warning

If sore throat is severe, persists for more than 2 days, is accompanied or followed by fever, headache, rash, nausea, or vomiting, consult a doctor promptly.

Do not use

- with any other drug containing acetaminophen (prescription or nonprescription). If you are not sure whether a drug contains acetaminophen, ask a doctor or pharmacist.
- if you are now taking a prescription monoamine oxidase inhibitor (MAOI) (certain drugs for depression, psychiatric or emotional conditions, or Parkinson's disease), or for 2 weeks after stopping the MAOI drug. If you do not know if your prescription drug contains an MAOI, ask a doctor or pharmacist before taking this product.

Ask a doctor before use if you have

- liver disease
- heart disease
- high blood pressure
- thyroid disease
- diabetes
- glaucoma
- a sodium-restricted diet
- trouble urinating due to enlarged prostate gland
- cough that occurs with too much phlegm (mucus)
- a breathing problem or chronic cough that lasts or as occurs with smoking, asthma, chronic bronchitis, or emphysema

Ask a doctor or pharmacist before use if you are

- taking sedatives or tranquilizers
- taking the blood thinning drug warfarin

When using this product

- do not use more than directed
- excitability may occur, especially in children
- marked drowsiness may occur
- avoid alcoholic drinks
- be careful when driving a motor vehicle or operating machinery
- alcohol, sedatives, and tranquilizers may increase drowsiness

Stop use and ask a doctor if

- you get nervous, dizzy or sleepless
- pain, nasal congestion, or cough gets worse or lasts more than 7 days
- fever gets worse or lasts more than 3 days
- redness or swelling is present
- new symptoms occur
- cough comes back or occurs with rash or headache that lasts. These could be signs of a serious condition.

PREGNANCY OR BREAST FEEDING

If pregnant or breast-feeding, ask a health professional before use.

Keep out of reach of children.

Overdose warning

In case of overdose, get medical help or contact a Poison Control Center right away.

Directions

- take only as directed
- do not exceed 8 softgels per 24 hours

adults & children 12 yrs & over | 2 softgels with water every 4 hrs
children 4 to under 12 yrs | ask a doctor
children under 4 yrs | do not use

Other information

- store at 20-25°C (68-77°F)
- protect from light, heat and moisture

Inactive ingredients

D&C yellow #10, FD&C blue #1, gelatin, glycerin, polyethylene glycol, povidone K30, propylene glycol, purified water, sodium hydroxide, sorbitol sorbitan solution, titanium dioxide

Questions?

Call toll free: 1-888-423-0139

PRINCIPAL DISPLAY PANEL - 24 Softgel Blister Pack Carton

NDC: 36800-827-24

*Compare to the active ingredients
in Vicks® Nyquil™ Severe Cold & Flu

MAXIMUM STRENGTH RELIEF
Night Time
Cold & Flu Relief
SEVERE

PAIN RELIEVER-FEVER REDUCER - ACETAMINOPHEN
COUGH SUPPRESSANT - DEXTROMETHORPHAN HBr
ANTIHISTAMINE - DOXYLAMINE SUCCINATE
NASAL DECONGESTANT - PHENYLEPHRINE HCl

• Headache, Fever, Sore Throat, Minor Aches & Pains
• Sinus Congestion & Pressure
• Runny Nose & Sneezing • Cough

24 SOFTGELS

actual size